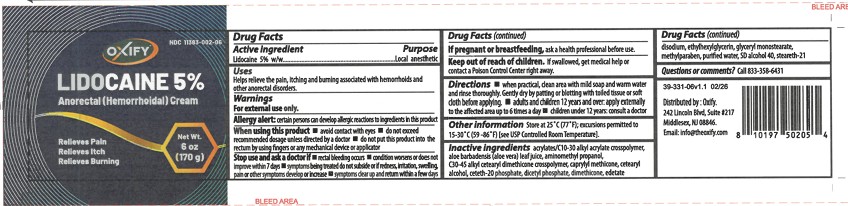 DRUG LABEL: Oxify
NDC: 11383-002 | Form: CREAM
Manufacturer: Weeks & Leo Compnay, INC.
Category: otc | Type: HUMAN OTC DRUG LABEL
Date: 20260217

ACTIVE INGREDIENTS: LIDOCAINE 50 mg/1 g
INACTIVE INGREDIENTS: ALPHA-TOCOPHEROL ACETATE; DIMETHICONE 350; GLYCERYL STEARATE; DICETYL PHOSPHATE; C30-45 ALKYL CETEARYL DIMETHICONE CROSSPOLYMER; ALOE BARBADENSIS LEAF JUICE; ISOPROPYL MYRISTATE; METHYLPARABEN; CETETH-20 PHOSPHATE; TROLAMINE; CETEARYL ALCOHOL; CAPRYLYL METHICONE; EDETATE DISODIUM ANHYDROUS; STEARETH-21; WATER; ETHYLHEXYLGLYCERIN; ACRYLATES/C10-30 ALKYL ACRYLATE CROSSPOLYMER (60000 MPA.S); PROPYLENE GLYCOL; BENZYL ALCOHOL

Oxify Lidocaine 5% Cream

ACTIVE INGREDIENT

Lidocaine 5% w/w

ASK DOCTOR

- rectal bleeding occurs
- condition worsens or does not improve within 7 days
- symptoms being treated do not subside or if redness, irritation, swelling, pain or other symptoms develop or increase
- symptoms clear up and return within a few days

KEEP OUT OF REACH OF CHILDREN

If swallowed, get medical help or contact a Poison Control Center right away.

PREGNANCY OR BREAST FEEDING

Ask a health professional before use.

PURPOSE

Local anesthetic

QUESTIONS

Call 833-358-6431

STOP USE

- rectal bleeding occurs
- condition worsens or does not improve within 7 days
- symptoms being treated do not subside or if redness, irritation, swelling, pain or other symptoms develop or increase
- symptoms clear up and return within a few days

WHEN USING

- Avoid contact with eyes
- do not exceed recommended dosage unless directed by a doctor
- do not put this product into the rectum by using fingers or any mechanical device or applicator

WARNINGS

For External use only

DOSAGE AND ADMINISTRATION

- when practical, clean area with mild soap and warm water and rinse thoroughly. Gently dry by patting or blotting with toiled tissue or soft cloth before applying
- adults and children 12 years and over: apply externally to the affected area up to 6 times a day
- children under 12 years: consult a doctor

STORAGE AND HANDLING

Store at 25°C (77°F); excursions permitted to 15-30°C (59-86°F) [see USP Controoled Room Temperature]

INDICATIONS AND USAGE

Helps relieve the pain, itching, and burning associated with hemorrhoids and other anorectal disorders

Allergy alert: certain persons can develop allergic reactions to ingredients in this product.

INACTIVE INGREDIENT

acrylates/C10-30 alkyl acrylate crosspolymer, aloe barbadensis (aloe vera) leaf juice, aminomethyl propanol, C30-45 alkyl cetearyl dimethicone crosspolymer, caprylyl methicone, cetearyl alcohol, ceteth-20 phosphate, dicetyl phosphate, dimethicone, edetate

RECENT MAJOR CHANGES

Changed Administration section to dosage and administration section

PACKAGE LABEL

Oxify

Lidocaine 5% Anorectal (Hemorrhoidal) Cream

Relieves Pain

Relieves Itch

Relieves Burning

Net Wt. 6 oz (170 g)